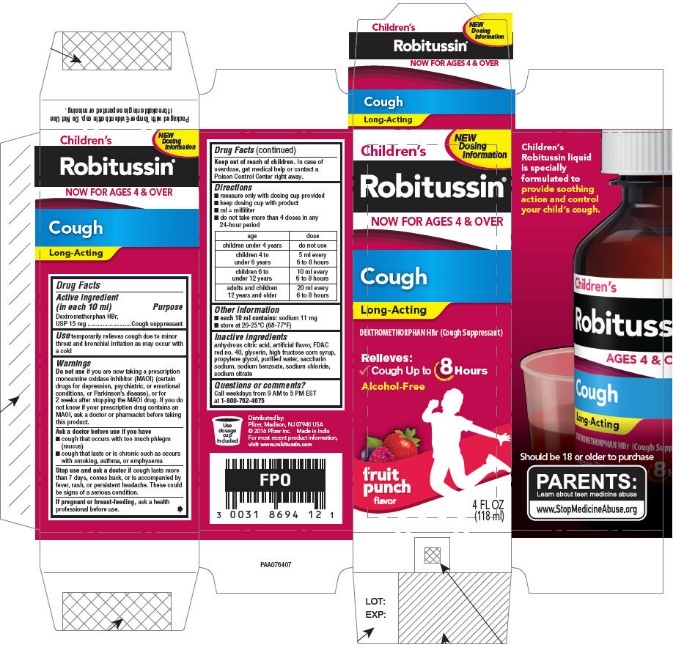 DRUG LABEL: Childrens Robitussin Cough Long-Acting
NDC: 0031-8694 | Form: LIQUID
Manufacturer: Haleon US Holdings LLC
Category: otc | Type: HUMAN OTC DRUG LABEL
Date: 20240317

ACTIVE INGREDIENTS: DEXTROMETHORPHAN HYDROBROMIDE 7.5 mg/5 mL
INACTIVE INGREDIENTS: ANHYDROUS CITRIC ACID; FD&C RED NO. 40; GLYCERIN; HIGH FRUCTOSE CORN SYRUP; PROPYLENE GLYCOL; WATER; SACCHARIN SODIUM; SODIUM BENZOATE; SODIUM CHLORIDE; SODIUM CITRATE, UNSPECIFIED FORM

DRUG FACTS

Active ingredient (in each 10 ml)

Dextromethorphan HBr, USP 15 mg

Purpose

Cough suppressant

Use

temporarily relieves cough due to minor throat and bronchial irritation as may occur with a cold

Warnings

DO NOT USE

Do not useif you are now taking a prescription monoamine oxidase inhibitor (MAOI) (certain drugs for depression, psychiatric, or emotional conditions, or Parkinson's disease), or for 2 weeks after stopping the MAOI drug. If you do not know if your prescription drug contains an MAOI, ask a doctor or pharmacist before taking this product.

Ask a doctor before use if you have

1. cough that occurs with too much phlegm (mucus)
2. cough that lasts or is chronic such as occurs with smoking, asthma, or emphysema

Stop use and ask a doctor ifcough lasts more than 7 days, comes back, or is accompanied by fever, rash, or persistent headache. These could be signs of a serious condition.

PREGNANCY OR BREAST FEEDING

If pregnant or breast-feeding,ask a health professional before use.

Keep out of reach of children.In case of overdose, get medical help or contact a Poison Control Center right away.

Directions

1. measure only with dosing cup provided
2. keep dosing cup with product
3. ml = milliliter
4. do not take more than 4 doses in any 24-hour period

age | dose
children under 4 years | do not use
children 4 to under 6 years | 5 ml every 6 - 8 hours
children 6 to under 12 years | 10 ml every 6 to 8 hours
adults and children 12 years and older | 20 ml every 6 to 8 hours

Other information

1. each 10 ml contains:sodium 11 mg
2. store at 20-25°C (68-77°F)

Inactive ingredients

anhydrous citric acid, artificial flavor, FD&C red no. 40, glycerin, high fructose corn syrup, propylene glycol, purified water, saccharin sodium, sodium benzoate, sodium chloride, sodium citrate

Questions or comments?

Call weekdays from 9 AM to 5 PM EST at 1-800-762-4675

Distributed by:
Pfizer, Madison, NJ 07940 USA

For most recent product information, visit
www.robitussin.com

PRINCIPAL DISPLAY PANEL

NEW
Dosing
Information

Children's
Robitussin®
NOW FOR AGES 4 & OVER

Cough

Long-Acting

DEXTROMETHORPHAN HBr (Cough Suppressant)

Relieves:

✓ Cough Up to 8 Hours

Alcohol-Free

fruit
punch
flavor

4 FL OZ
(118 ml)